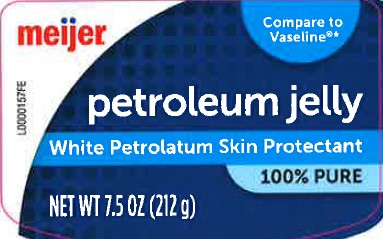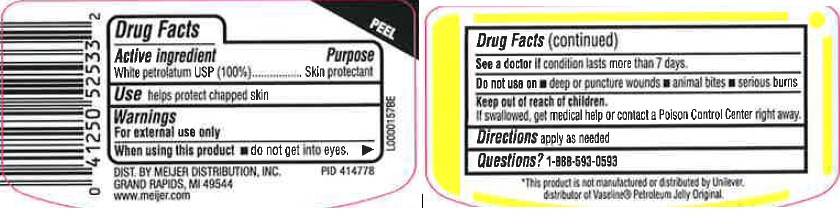 DRUG LABEL: Petroleum Skin Protectant
NDC: 41250-069 | Form: JELLY
Manufacturer: Meijer, Inc.
Category: otc | Type: HUMAN OTC DRUG LABEL
Date: 20260219

ACTIVE INGREDIENTS: PETROLATUM 1 g/1 g

Meijer 069.001/069AA
Petroleum Jelly

Active ingredient

White petrolatum USP (100%)

Purpose

Skin protectant

Use

helps protect chapped skin

Warnings

For external use only

When using this product

- do not get into eyes

See a doctor if

condition lasts more than 7 days.

Do not use on

- deep or puncture wounds
- animal bites
- serious burns

Keep out of reach of children.

If swallowed, get medical help or contact a Poison Control Center right away.

Directions

apply as needed

Inactive ingredient

None

INACTIVE INGREDIENT

None

Dislcaimer

*This product is not manufactured or distributed by Unilever, distributor of Vaseline® Petroleum Jelly Original.

Adverse Reactions

DIST. BY MEIJER DISTRIBUTION, INC.

GRAND RAPIDS, MI 49544

www.meijer.com

principal display panel

Meijer®

Compare to Vaseline ®*

Petroleum Jelly

White Petrolatum SKin Protectant

100% Pure

NET 7.5 OZ (212 g)